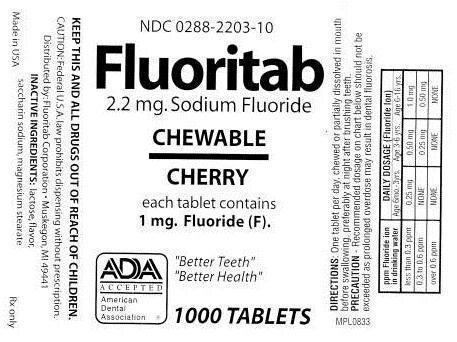 DRUG LABEL: FLUORITAB CHEWABLE
NDC: 0288-2203 | Form: TABLET, CHEWABLE
Manufacturer: Fluoritab Corporation
Category: prescription | Type: HUMAN PRESCRIPTION DRUG LABEL
Date: 20121029

ACTIVE INGREDIENTS: SODIUM FLUORIDE 1 mg/1 1
INACTIVE INGREDIENTS: LACTOSE; SACCHARIN SODIUM ANHYDROUS; MAGNESIUM STEARATE

ACTIVE INGREDIENT

CONTAINS: 2.2 MG SODIUM FLUORIDE

EACH TABLET CONTAINS 1 MG FLUORIDE

PPM FLUORIDE IONDAILY DOSAGE

IN DRINKING WATERAGE 6 MO. – 3 YRS.AGE 3-6 YRS.AGE 6-16 YRS.

LESS THAN 0.3 PPM0.25 MG 0.50 MG1 MG

0.3 TO 0.6 PPMNONE 0.25 MG 0.50 MG

OVER 0.6 PPMNONENONENONE

KEEP OUT OF REACH OF CHILDREN.

WARNINGS

CAUTION: FEDERAL (U.S.A.) LAW PROHIBITS DISPENSING WITHOUT PRESCRIPTION.

INDICATIONS AND USAGE

DIRECTIONS: ONE TABLET PER DAY, CHEWED OR PARTIALLY DISSOLVED IN MOUTH BEFORE SWALLOWING, PREFERABLY AT NIGHT AFTER BRUSHING TEETH.

INACTIVE INGREDIENT

INACTIVE INGREDIENTS: LACTOSE, FLAVOR, SACCHARIN SODIUM, MAGNESIUM STEARATE

WARNINGS AND PRECAUTIONS

PRECAUTION -RECOMMEND DOSAGE ON CHART BELOW SHOULD NOT BE EXCEEDED AS PROLONGED OVERDOSE MAY RESULT IN DENTAL FLUOROSIS.